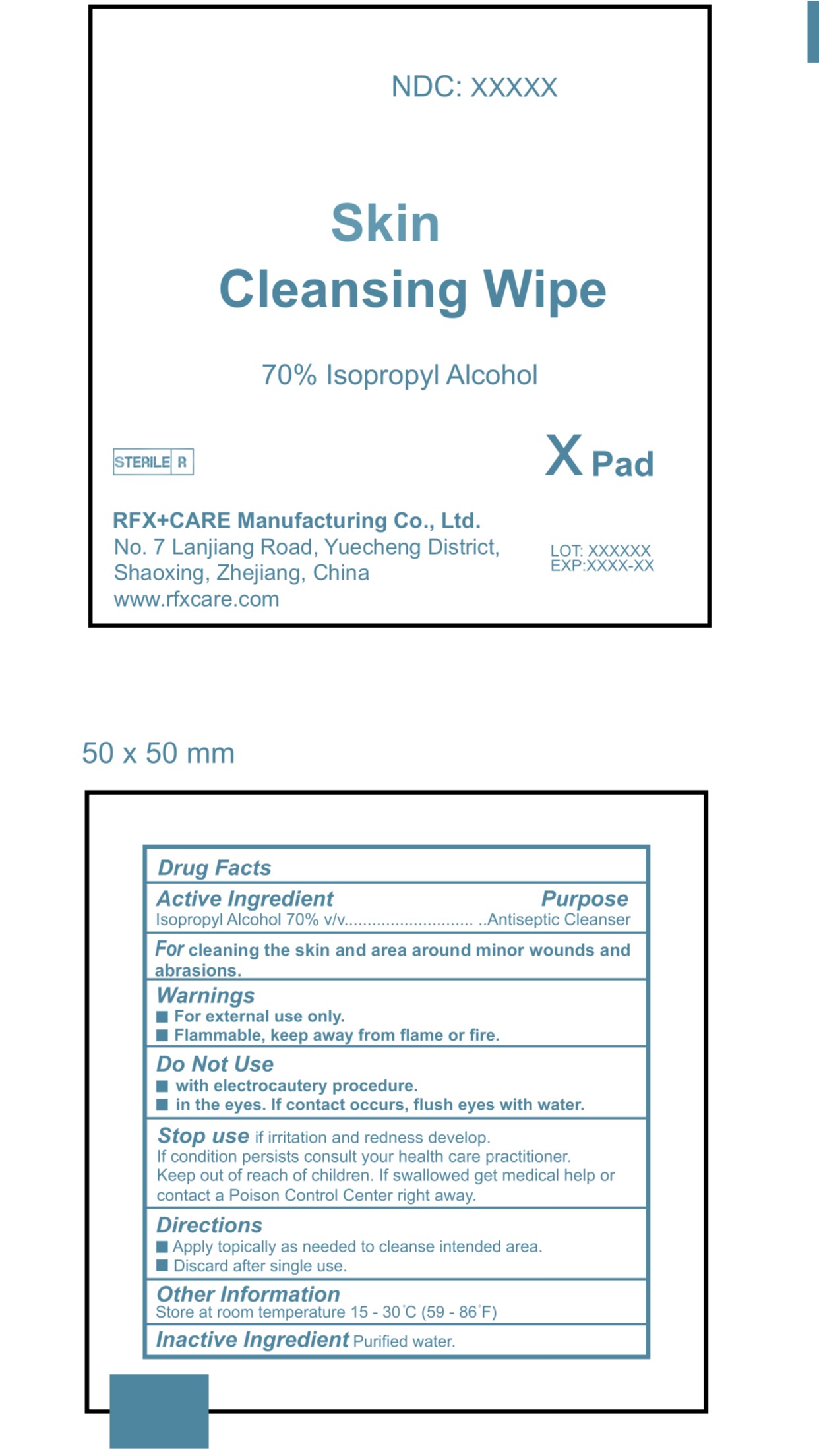 DRUG LABEL: Skin Cleansing Wipe
NDC: 82283-001 | Form: SOLUTION
Manufacturer: RFX+CARE Manufacturing Co., Ltd.
Category: otc | Type: HUMAN OTC DRUG LABEL
Date: 20231129

ACTIVE INGREDIENTS: ISOPROPYL ALCOHOL 70 mL/100 mL
INACTIVE INGREDIENTS: WATER

82283-001

Active Ingredient(s)

Isopropyl Alcohol 70% v/v

Purpose

Antiseptic Cleanser

Use

For cleaning the skin and area around minor wounds and abrasions

Warnings

For external use only.

Flammable. Keep away from flame or fire

Do not use:

- with electrocautery procesures
- in the eyes. If contact occurs flush eyes with water

Stop use:

- if irritation and redness develop
- if condition persists, consult your health care practitioner

Keep out of reach of children. If swallowed, get medical help or contact a Poison Control Center right away

Directions

Apply topically as needed to cleanse intended area

Discard affter single use

Other information

Store at room temperature 15-30C (59-86F)

Inactive ingredients

Purified Water